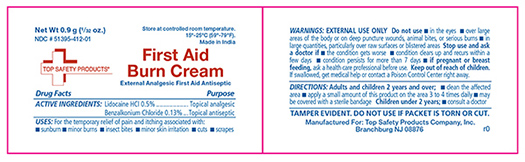 DRUG LABEL: Top Safety First Aid Burn Cream
NDC: 51395-412 | Form: CREAM
Manufacturer: Top Safety Products Company Inc
Category: otc | Type: HUMAN OTC DRUG LABEL
Date: 20190312

ACTIVE INGREDIENTS: LIDOCAINE HYDROCHLORIDE 0.5 g/100 g; BENZALKONIUM CHLORIDE 0.13 g/100 g
INACTIVE INGREDIENTS: ISOPROPYL MYRISTATE; METHYLCELLULOSE (25 MPA.S); CETOSTEARYL ALCOHOL; GLYCERYL MONOSTEARATE; DIMETHICONE; CETETH-20; BUTYLATED HYDROXYTOLUENE; METHYLPARABEN SODIUM; PROPYLPARABEN SODIUM; GLYCERIN; EDETATE SODIUM; WATER

TS-605-365T Top Safety First Aid Burn Cream NDC 51395-412-01

Active Ingredients

Active Ingredient Purpose

Lidocaine HCL 0.5% Topical Analgesic

Benzalkonium Chloride 0.13% Topical Antiseptic

Purpose

Temporary relief of pain and itching.

Uses

For temporary relief of pain and itching associated with:

- Sunburn
- Minor burns,
- Insect bites,
- Minor skin irritation,
- Cuts and
- Scrapes

Warnings

FOR EXTERNAL USE ONLY

KEEP OUT OF REACH OF CHILDREN

If swallowed, get medical help or contact a Poison Control Center right away.

Stop Use

Stop Use and ask a doctor:

- If condition worsens or,
- if symptoms persist for more than 7 days or clear up and occur again in a few days.
- If pregnant or breast feeding, ask a health professional before use.

Do Not Use

- In the eyes
- Over large areas of the body or on deep puncture wounds, animal bites or serious burns.
- In large quantities, particularly over raw surfaces or blistered areas.

Directions

Adults and children 2 years and over:

- clean the affected area
- apply a small amount of this product on the area 3 or 4 times daily.
- may be covered with a sterile bandage

Children under 2 years

- consult a doctor

Inactive ingredients

Buttylated hydroxy toluene, Cetomacrogol, Cetostearyl alcohol, Dimethicone, Glycerine, Glyceryl monostearate, Isopropyl myristate, Methylcellulose, Purified water, Sodium EDTA, Sodium methylparaben, Sodium propylparaben

Other Information

- store in a cool, dry area
- 59o to 79o F (15o to 25o C)
- Tamper evident sealed packets do not use any open or torn packets

Principal Display Panel

Top Safety First Aid Burn Cream

Top Safety.jpg